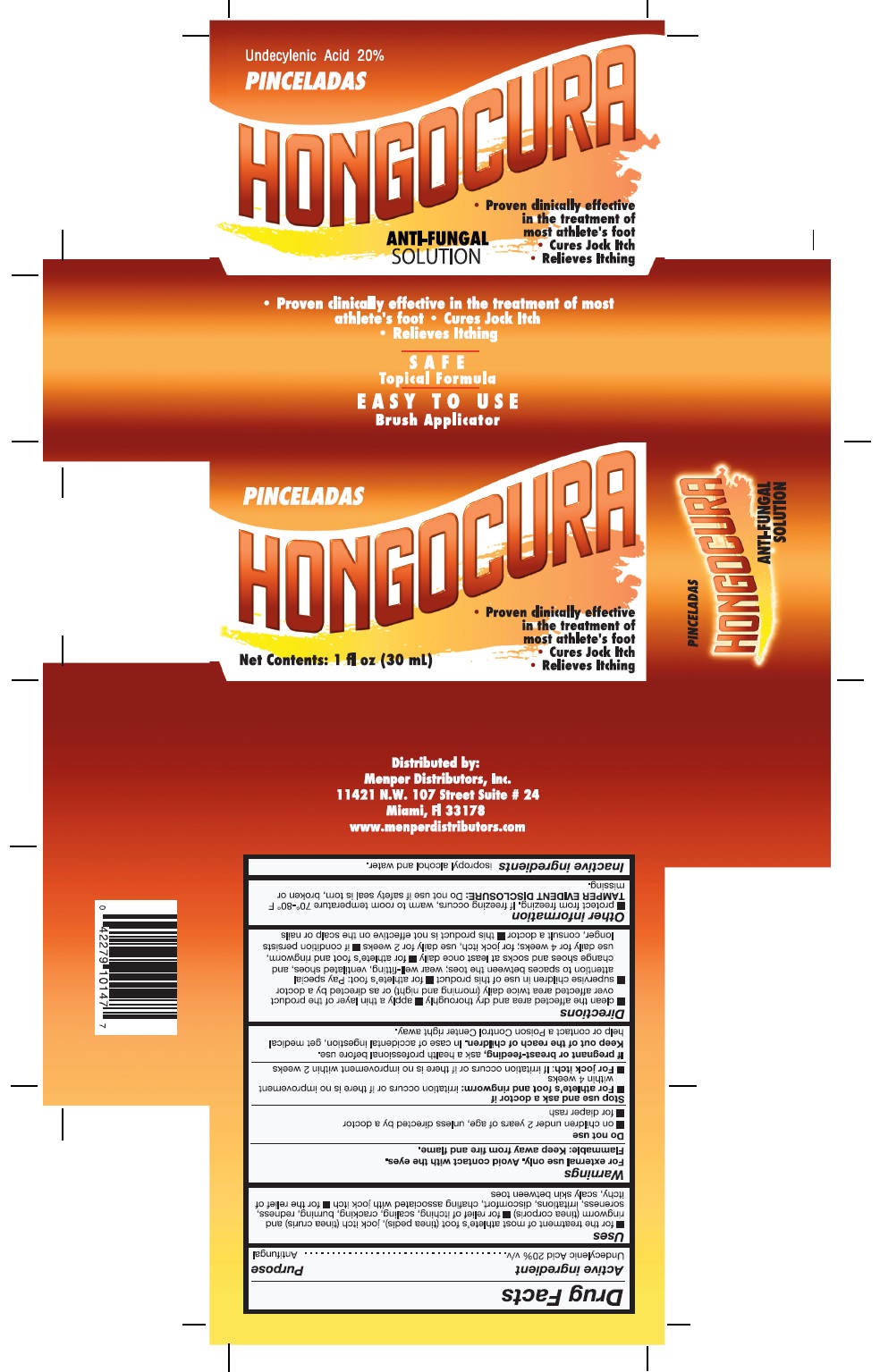 DRUG LABEL: Hongocura Pinceladas
NDC: 53145-019 | Form: LIQUID
Manufacturer: Menper Distributors, Inc.
Category: otc | Type: HUMAN OTC DRUG LABEL
Date: 20250722

ACTIVE INGREDIENTS: UNDECYLENIC ACID 200 mg/1 mL
INACTIVE INGREDIENTS: WATER; ISOPROPYL ALCOHOL

Hongocura Pinceladas

Active ingredient

Undecylenic Acid 20%.................Antifungal

Purpose

Anti-Fungal

Uses

- for the treatment of most athlete’s foot (tinea pedis), jock itch (tinea curis) and ringworm (tinea corporis)
- for relief if itching, scaling, cracking, burning, redness, soreness, irritations, discomfort, chafing associated with jock itch
- for the relief of itch, scaly skin between toes

Warnings

For external use only . Avoid contact with the eyes.

Flammable: Keep away from fire and flames.

Do not use

- on children under 2 years of age, unless directed by a docyor
- for diaper rash

Stop use and ask a doctor if

for athlete's foot and ringworm: irritation occurs or if there is no improvement within 4 weeks.

ZFor jock itch: If irritation occurs or if there is no improvement within two weeks.

if pregnant or breast-feeding

ask a health professional before use

Keep out of the reach of children.

In case of accidental ingestion, get medical help or contact a Poiso Control Center right away.

Directions

- clean the affected area and dry thoroughly
- apply a thin layer of the product over affected area twice daily (morning and night)or as directed by a doctor
- supervise children in use of this product
- for athlete's foot: Pay special attention to spaces between the toes; wear well-fitting, ventilated shoes, and change shoes and socks at least once daily.
- for athlete's foot and ringworm, use daily for 4 weeks; for jock itch, use daily for 2 weeks
- if condition persists longer, consult a doctor
- this product is not effective on th e scalp or nails

Othe information

- protect from freezing, If freezing occurs, warm to room tewmperature 70°-80° F

Tamper Evident Disclosure: Do not use if safety seal is torn, broken or missing.

Inactive Ingredients

isopropyl alcohol and water.